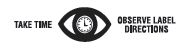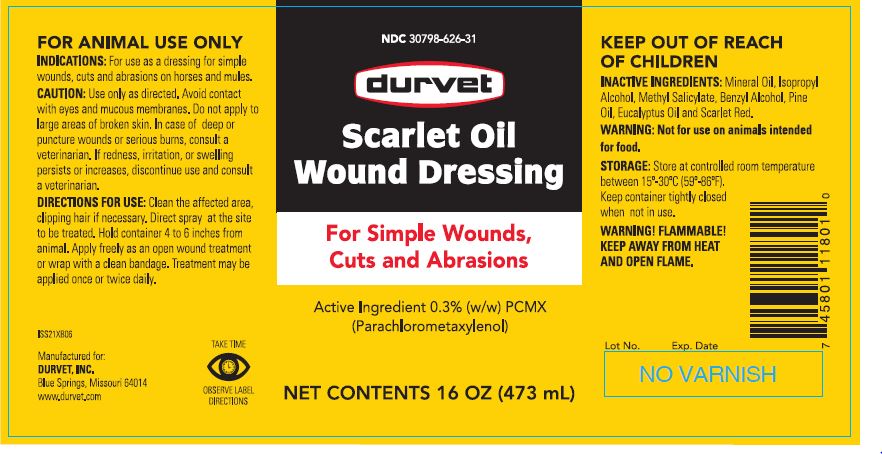 DRUG LABEL: Scarlet Oil
NDC: 30798-626 | Form: SOLUTION
Manufacturer: Durvet, Inc.
Category: animal | Type: OTC ANIMAL DRUG LABEL
Date: 20260223

ACTIVE INGREDIENTS: CHLOROXYLENOL 2.5 mg/1 mL

SCARLET OIL WOUND DRESSING

PURPOSE

For Simple Wounds, Cuts and Abrasions

Active Ingredient 0.3% (w/w) PCMX (Parachlorometaxylenol)

WHEN USING

FOR ANIMAL USE ONLY

INDICATIONS:

For use as a dressing for simple wounds, cuts and abrasions on horses and mules.

CAUTION:

Use only as directed. Avoid contact with eyes and mucous membranes. Do not apply to large areas of broken skin. In case of deep or puncture wounds or serious burns, consult a veterinarian. If redness, irritation, or swelling persists or increases, discontinue use and consult a veterinarian.

DIRECTIONS FOR USE:

Clean the affected area, clipping hair if necessary. Direct spray at the site to be treated. Hold container 4 to 6 inches from animal. Apply freely as an open wound treatment or wrap with a clean bandage. Treatment may be applied once or twice daily.

KEEP OUT OF REACH OF CHILDREN

INACTIVE INGREDIENTS:

Mineral Oil, Isopropyl Alcohol, Methyl Salicylate, Benzyl Alcohol, Pine Oil, Eucalyptus Oil and Scarlet Red.

FOOD SAFETY WARNING

WARNING: Not for use on animals intended for food.

STORAGE:

Store at controlled room temperature between 15º-30ºC (59º-86ºF). Keep container tightly closed when not in use.

WARNINGS AND PRECAUTIONS

WARNING! FLAMMABLE! KEEP AWAY FROM HEAT AND OPEN FLAME.

Net Contents:

16 OZ (473 mL)

INFORMATION FOR OWNERS/CAREGIVERS

Manufactured for:
DURVET, INC.
Blue Springs, Missouri 64014 Rev. 04-16

www.durvet.com